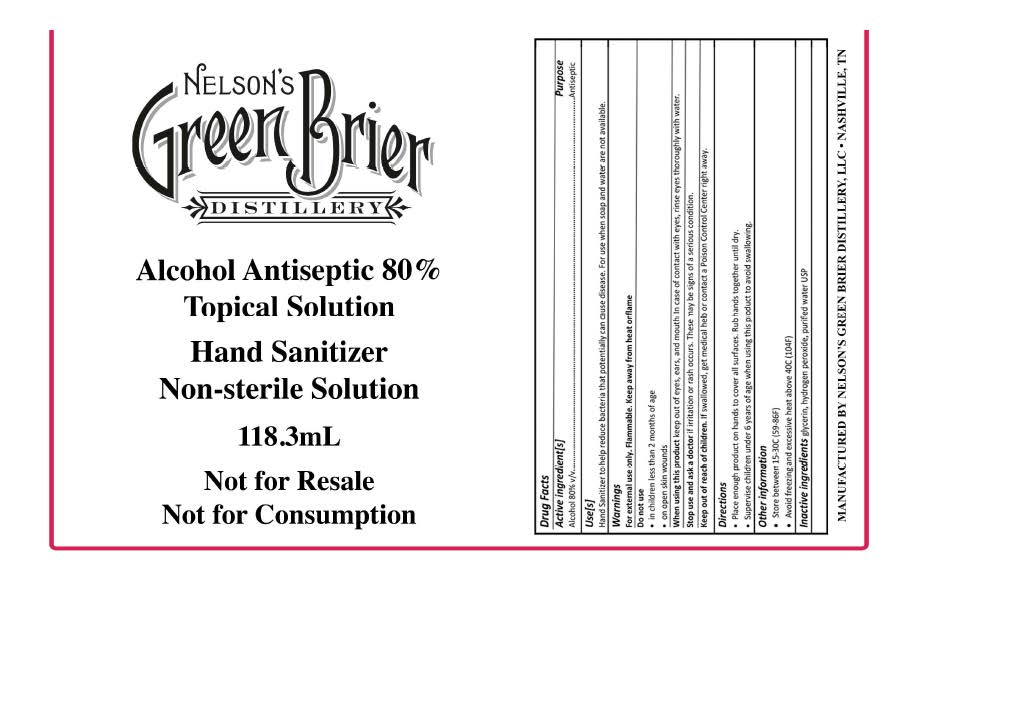 DRUG LABEL: Nelsons Green Brier Hand Sanitizer
NDC: 74204-003 | Form: LIQUID
Manufacturer: Nelson's Green Brier Distillery, LLC
Category: otc | Type: HUMAN OTC DRUG LABEL
Date: 20200417

ACTIVE INGREDIENTS: ALCOHOL 94.64 mL/118.3 mL
INACTIVE INGREDIENTS: HYDROGEN PEROXIDE 0.12 mL/118.3 mL; GLYCEROL FORMAL 1.77 mL/118.3 mL; WATER 21.77 mL/118.3 mL

Active Ingredients

Active Ingredient[s]/ Purpose

Alcohol 80% v/v..........Antiseptic

Do Not Use

- in children less than 2 months of age
- on open skin wounds

Purpose:

Use[s]

Hand Sanitizer to help reduce bacteria potentially can cause disease. For use when soap and water are not available.

Stop Use

Stop use and ask a doctor if irritation or rash occurs. These may be signs of a serious condition.

When Using

When using this product keep out of eyes, ears and mouth. In case of contact with eyes, rinse eyes thoroughly with water.

Other Information

- Store between 15- 30C (59-86F)
- Avoid freezing and excessive heat above 40C (104F)

Warnings and Precautions

Warnings

For external use only. Flammable. Keep away from heat or flame.

Inacative Ingredients Section

Inactive ingredients glycerin, hydrogen peroxide, purified water USP

Dosage and Administration

Directions

- Place enough product on hands to cover all surfaces. Rub hands together until dry.
- Supervise children under 6 years when using this product to avoid swallowing.

Warning

For external use only. Flammable. Keep away from heat or flame

Indications & Usage Section

Hand Sanitizer to help reduce bacteria potentially can cause disease. For use when soap and water are not available.

Keep out of reach of children. If swallowed, get medical help or contact Poison Control Center right away.

Recent Major Changes Section

N/A Original Label

When substantive labeling changes have been made to any of the following sections of the FPI within the preceding 12 months, the heading(s) of the changed section(s) must be listed in Highlights under the heading Recent Major Changes (§ 201.57(a)(5)):

• Boxed Warning
• Indications and Usage
• Dosage and Administration
• Contraindications
• Warnings and Precautions

Changes that must not be listed in Recent Major Changes include:

• Changes to sections other than the five listed above
• Changes that are not substantive (i.e., minor revisions such as correcting typographical errors or grammatical changes)
• Changes resulting from converting to the PLR format alone

a. What must be included ?
Each listing must include the section heading, the subsection heading (if appropriate), identifying number of the corresponding changed section or subsection, and the date on which the change was incorporated in the labeling (i.e., date the supplement was approved) in month/year format (e.g., 6/2010 or Jun 2010) (§ 201.57(a)(5)).

Primary Display Panel

Nelson's

Green Brier

Distillery

Alcohol Antiseptic 80%

Topical Solution

Hand Sanitizer

Non-sterile Solution

118.3mL

Not for Resale

Not for Consumption